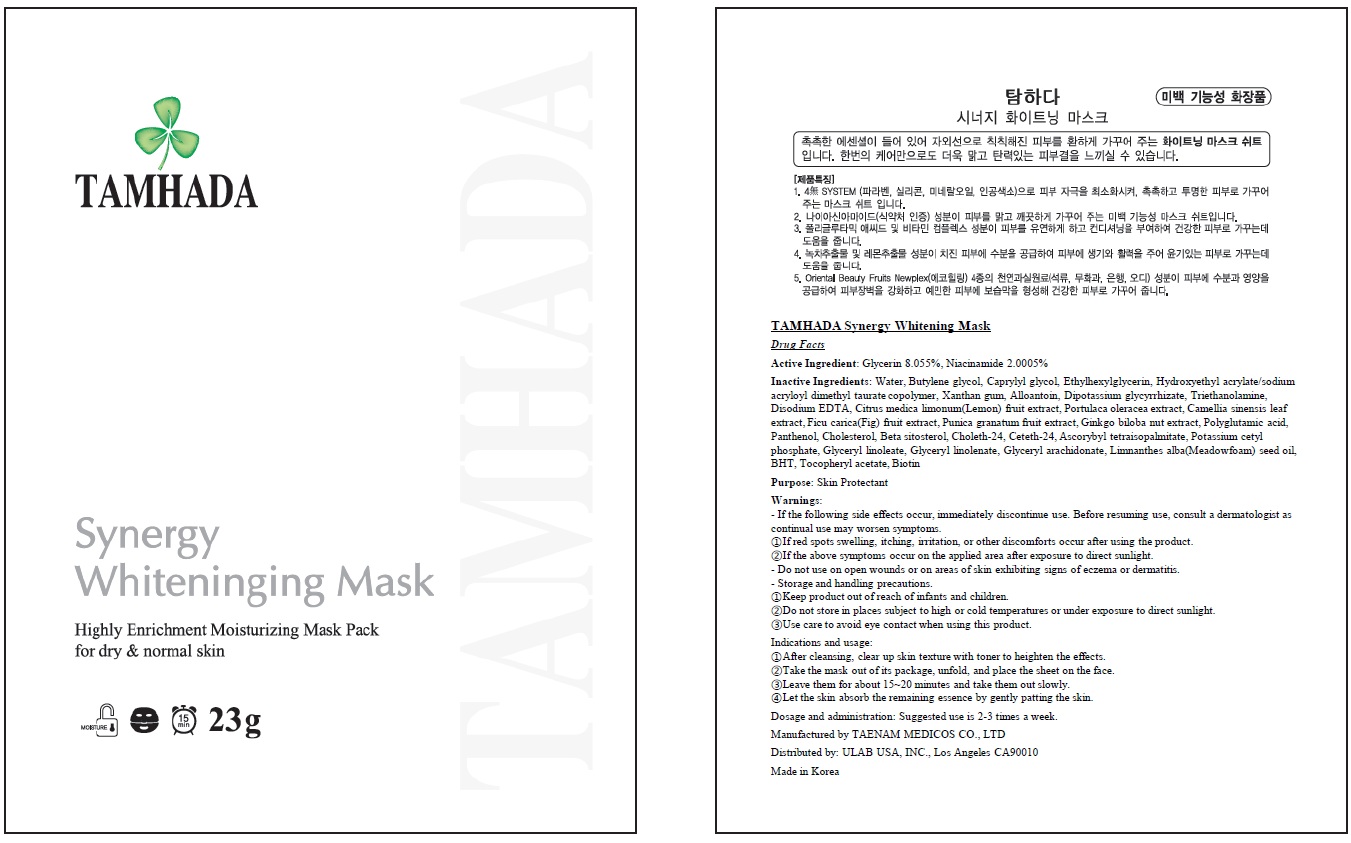 DRUG LABEL: TAMHADA Synergy Whitening Mask
NDC: 70894-050 | Form: PATCH
Manufacturer: TAENAM MEDICOS CO., LTD
Category: otc | Type: HUMAN OTC DRUG LABEL
Date: 20161025

ACTIVE INGREDIENTS: Glycerin 1.85 g/23 g; Niacinamide 0.46 g/23 g
INACTIVE INGREDIENTS: Water; Butylene glycol

ACTIVE INGREDIENT

Active Ingredient: Glycerin 8.055%, Niacinamide 2.0005%

INACTIVE INGREDIENT

Inactive Ingredients: Water, Butylene glycol, Caprylyl glycol, Ethylhexylglycerin, Hydroxyethyl acrylate/sodium acryloyl dimethyl taurate copolymer, Xanthan gum, Alloantoin, Dipotassium glycyrrhizate, Triethanolamine, Disodium EDTA, Citrus medica limonum(Lemon) fruit extract, Portulaca oleracea extract, Camellia sinensis leaf extract, Ficu carica(Fig) fruit extract, Punica granatum fruit extract, Ginkgo biloba nut extract, Polyglutamic acid, Panthenol, Cholesterol, Beta sitosterol, Choleth-24, Ceteth-24, Ascorybyl tetraisopalmitate, Potassium cetyl phosphate, Glyceryl linoleate, Glyceryl linolenate, Glyceryl arachidonate, Limnanthes alba(Meadowfoam) seed oil, BHT, Tocopheryl acetate, Biotin

PURPOSE

Purpose: Skin Protectant

WARNINGS

Warnings: - If the following side effects occur, immediately discontinue use. Before resuming use, consult a dermatologist as continual use may worsen symptoms. ①If red spots swelling, itching, irritation, or other discomforts occur after using the product. ②If the above symptoms occur on the applied area after exposure to direct sunlight. - Do not use on open wounds or on areas of skin exhibiting signs of eczema or dermatitis. - Storage and handling precautions. ①Keep product out of reach of infants and children. ②Do not store in places subject to high or cold temperatures or under exposure to direct sunlight. ③Use care to avoid eye contact when using this product.

KEEP OUT OF REACH OF CHILDREN

Keep product out of reach of infants and children.

INDICATIONS & USAGE

Indications and usage: ①After cleansing, clear up skin texture with toner to heighten the effects. ②Take the mask out of its package, unfold, and place the sheet on the face. ③Leave them for about 15~20 minutes and take them out slowly. ④Let the skin absorb the remaining essence by gently patting the skin.

DOSAGE & ADMINISTRATION

Dosage and administration: Suggested use is 2-3 times a week.